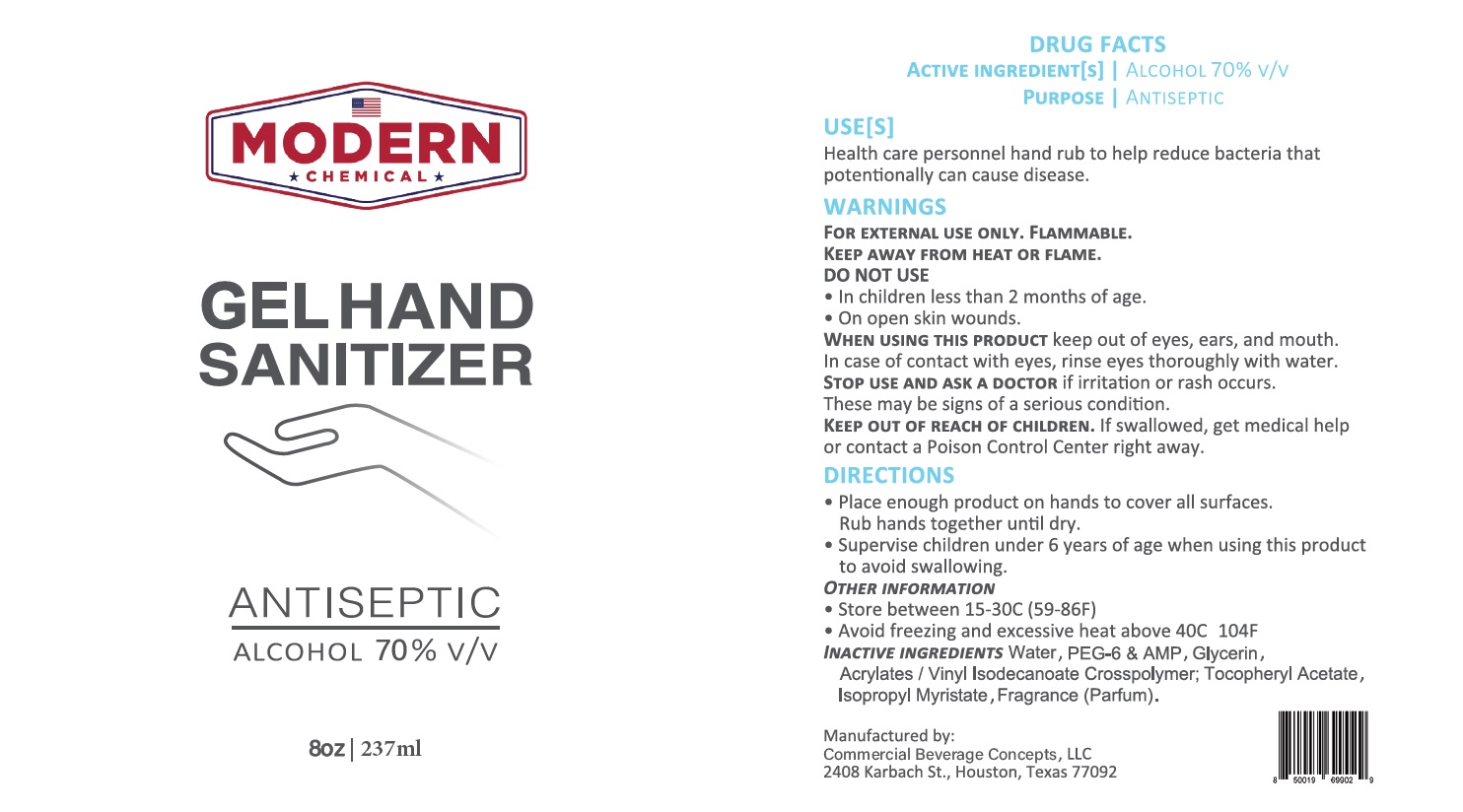 DRUG LABEL: Hand Sanitizer
NDC: 75594-870 | Form: GEL
Manufacturer: Commercial Beverage Concepts, LLC
Category: otc | Type: HUMAN OTC DRUG LABEL
Date: 20200610

ACTIVE INGREDIENTS: ALCOHOL 0.7 mL/1 mL
INACTIVE INGREDIENTS: POLYETHYLENE GLYCOL 300; ADENOSINE PHOSPHATE; GLYCERIN; ACRYLATES/VINYL ISODECANOATE CROSSPOLYMER (10000 MPA.S NEUTRALIZED AT 0.5%); .ALPHA.-TOCOPHEROL ACETATE; ISOPROPYL MYRISTATE

Gel Hand Sanitizer 70%, 237mL

ACTIVE INGREDIENT [S]

ALCOHOL 70% v/v

PURPOSE

ANTISEPTIC

USE[S]

Health care personnel hand rub to help reduce baceria that potentionally can cause disease.

WARNINGS

FOR EXTERNAL USE ONLY. FLAMMABLE. KEEP AWAY FROM HEAT OR FLAME.

DO NOT USE

- In children less than 2 months of age.
- On open skin wounds.

WHEN USING THIS PRODUCT

keep out of eyes, ears, and mouth. In case of contact with eyes, rinse eyes thoroughly with water.

STOP USE AND ASK A DOCTOR

if irritation or rash occurs. These may be signs of a serious condition.

KEEP OUT OF REACH OF CHILDREN.

If swallowed, get medical help or contact a Poison Control Center right away.

DIRECTIONS

- Place enough product on hands to cover all surfaces. Rub hands together until dry.
- Suprevise children under 6 years of age when using this product to avoid swallowing.

OTHER INFORMATION

- Store between 15-30C (59-86F)
- Avoid freezing and excessive heat above 40C 104F

INACTIVE INGREDIENTS

PEG-6 & AMP, Glycerin, Acrylates / Vinyl Isodecanoate Crosspolymer, Tocopheryl Acetate, Isopropyl Myristate, Fragrance (Parfum).